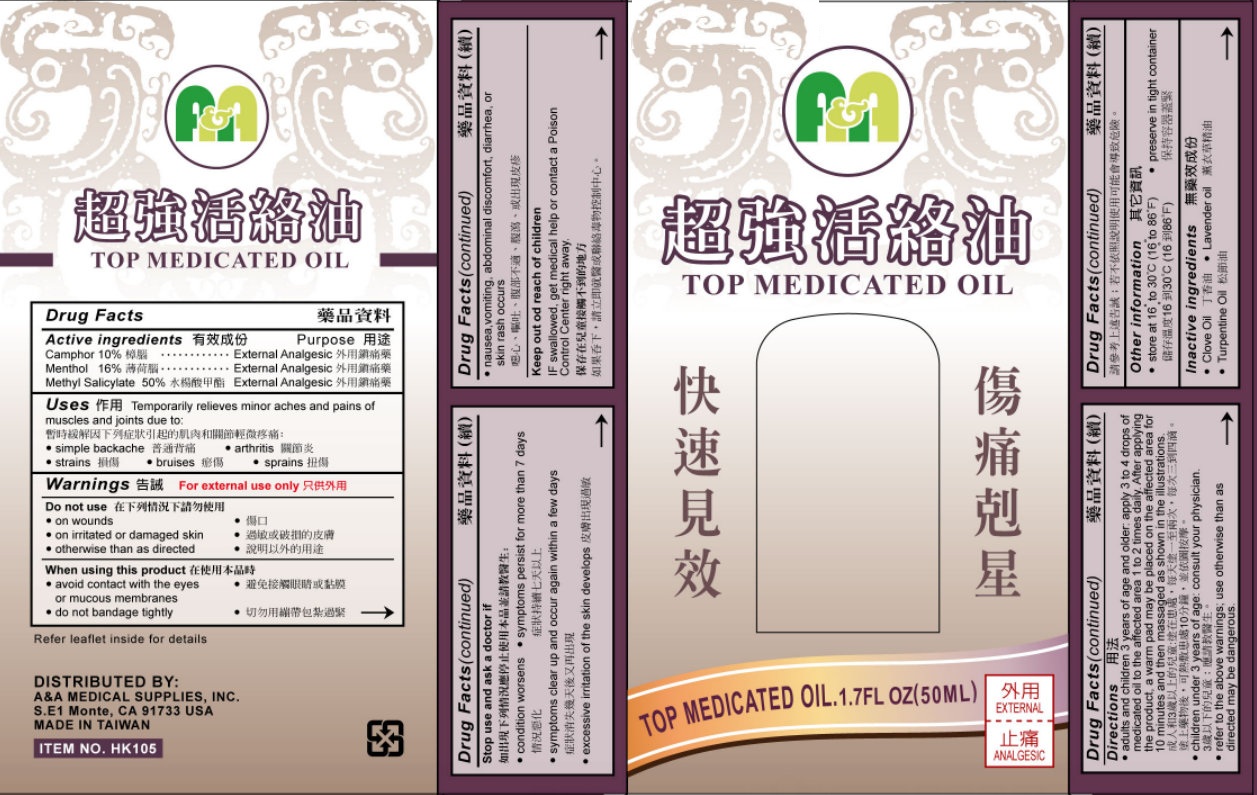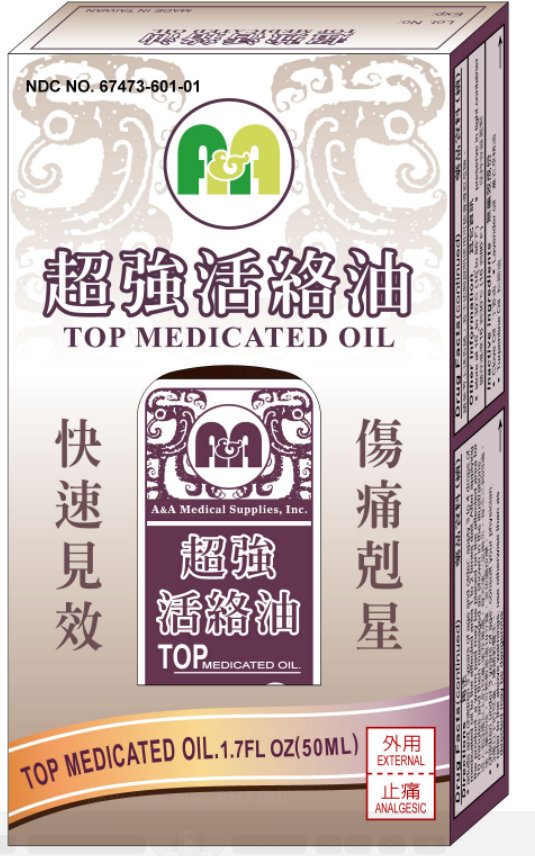 DRUG LABEL: Top Medicated
NDC: 50943-001 | Form: OIL
Manufacturer: A&A Medical Supplies
Category: otc | Type: HUMAN OTC DRUG LABEL
Date: 20120601

ACTIVE INGREDIENTS: CAMPHOR (NATURAL) 10 mL/100 mL; MENTHOL 16 mL/100 mL; METHYL SALICYLATE 50 mL/100 mL
INACTIVE INGREDIENTS: CLOVE OIL; LAVENDER OIL; TURPENTINE OIL

Top Medicated Oil

Active Ingredients

Camphor 10%

Menthol 16%

Methyl Salicylate 50%

Purpose

External Analgesic

Uses

Temporarily relieves minor aches and pains of muscles and joints due to:

- simple backache
- strains
- bruises
- arthritis
- sprains

Warnings

For external use only

Do not use

- on wounds
- on irritated or damaged skin
- otherwise than as directed

When using this product

- avoid contact with the eyes or mucous membranes
- do not bandage tightly

Stop use and ask a doctor if:

- condition worsens
- symptoms persist for more than 7 days
- symptoms clear up and occur again within a few days
- excessive irritation of the skin develops
- nausea, vomiting, abdominal discomfort, diarrhea, or skin rash occurs

Keep out of reach of children

IF swallowed, get medical help or contact a Poison Control Center right away.

Directions

- adults and children 3 years of age and older: apply 3 to 4 drops of medicated oil to the affected area 1 to 2 times daily. After applying the product, a warm pad may be placed on the affected area for 10 minutes and then massaged as shown in the illustrations.
- children under 3 years of age: consult your physician.
- refer to the above warnings; use otherwise than as directed may be dangerous.

Other Information

- store at 16 to 30 degrees C (16 to 86 degrees F)
- preserve in tight container

Inactive Ingredients

- Clove Oil
- Lavender Oil
- Turpentine Oil